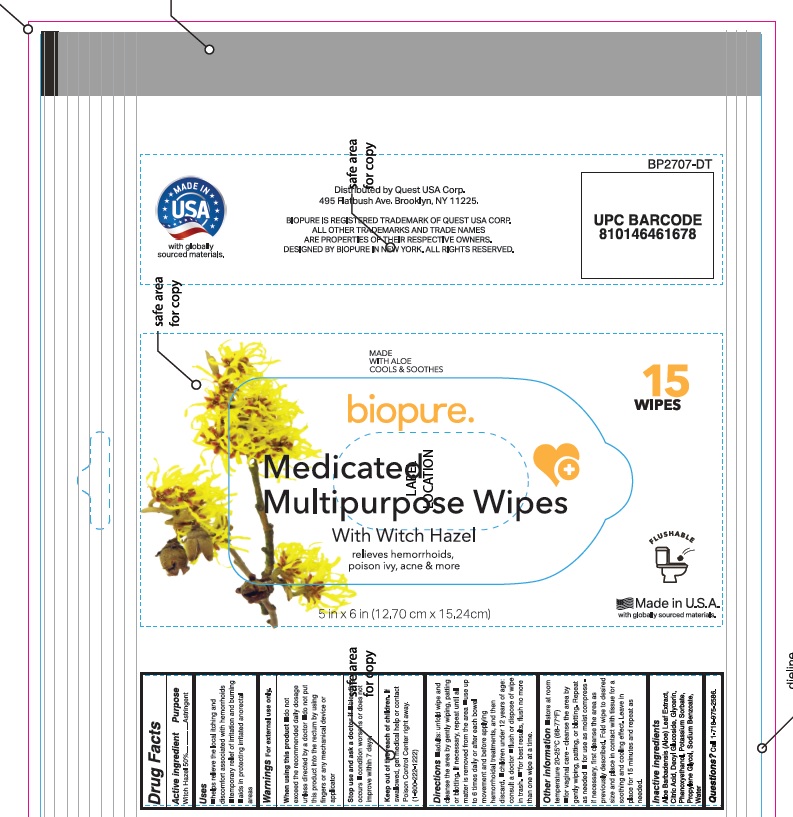 DRUG LABEL: Medicated Multipurpose Wipes
NDC: 78691-050 | Form: PATCH
Manufacturer: QUEST USA CORP.
Category: otc | Type: HUMAN OTC DRUG LABEL
Date: 20251205

ACTIVE INGREDIENTS: WITCH HAZEL 50 mg/100 mg
INACTIVE INGREDIENTS: PROPYLENE GLYCOL; SODIUM BENZOATE; PHENOXYETHANOL; WATER; ALOE VERA LEAF; CITRIC ACID MONOHYDRATE; DECYL GLUCOSIDE; GLYCERIN; POTASSIUM SORBATE

Active Ingredient

Witch Hazel 50%

Purpose

Astringent

Uses

helps relieve the local itching and discomfort associated with hemmorhoids

temporary relief of irritation and burning

aids in protecting irritated anorectal areas

Warnings

For external use only

When using this product

- do not exceed the recommended daily dosage unless directed by a doctor
- do not put this product into the rectum by using fingers or any mechanical device or applicator

Stop use and ask a doctor if

- bleeding occurs
- condition worsens or does not improve within 7 days

Keep Out Of Reach of Children

If swallowed, get medical help or contact Poison Control Center right away. (1-800-222-1222)

Directions

Adults

- unfold wipe and cleanse the area by gently wiping, patting or blotting. If necessary, repeat until all matter is removed from the area.
- use upto 6 times daily or after each bowel movement and before applying hemorrhoidal treatments and then discard.
- children under 12 years of age consult a doctor
- flush or dispose of wipe in trash
  - for best results flush no more than one wipe at a time

Other Information

- store at room temperature 20-25ºC (68-77ºF)
- for vaginal care - cleanse the area by gently wiping, patting or blotting. Repeat as needed.
- for use as moist compress if necessary, first cleanse the area as previously described. Fold wipe to desired size and place in contact with tissue for a soothing or cooling effect. Leave in place for 15 minutes and repeat as needed.

Inactive Ingredients

Aloe Barbadensis (Aloe) Leaf Extract, Citric Acid, Decyl Glucoside, Glycerin, Phenoxyethanol, Potassium Sorbate, Propylene Glycol, Sodium Benzoate, Water

Questions?

Call 1-718-975-2586

Principal Display Panel

NDC 78691-050-15

Biopure

Medicated Multipurpose Wipes With Witch Hazel

relieves hemorrhoids, poison ivy, acne and more

MADE WITH ALOE COOLS & SOOTHES

Made in U.S.A. with globally sourced materials

5 in X 6 in (12.70 cm X 15.24 cm)

15 WIPES